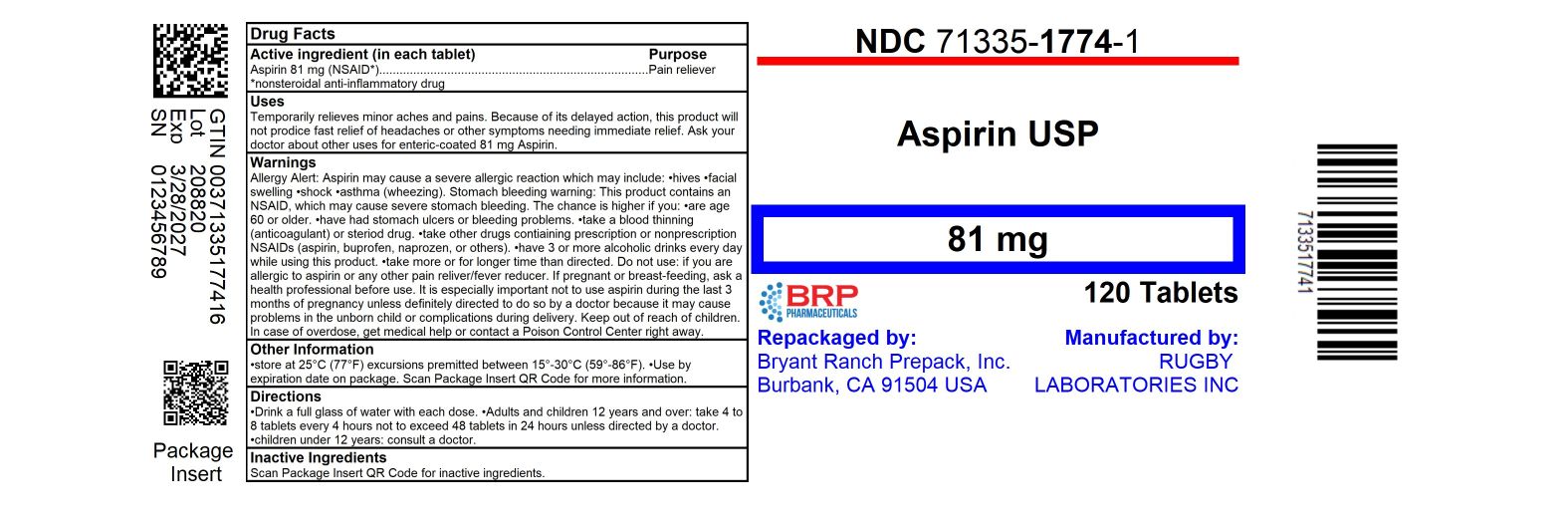 DRUG LABEL: Aspirin 81 mg
NDC: 71335-1774 | Form: TABLET, COATED
Manufacturer: Bryant Ranch Prepack
Category: otc | Type: HUMAN OTC DRUG LABEL
Date: 20250331

ACTIVE INGREDIENTS: ASPIRIN 81 mg/1 1
INACTIVE INGREDIENTS: D&C YELLOW NO. 10; SILICON DIOXIDE; METHACRYLIC ACID - ETHYL ACRYLATE COPOLYMER (1:1) TYPE A; TALC; TITANIUM DIOXIDE; TRIETHYL CITRATE; SODIUM BICARBONATE; SODIUM LAURYL SULFATE; POVIDONE, UNSPECIFIED; MICROCRYSTALLINE CELLULOSE; STEARIC ACID; STARCH, CORN

Aspirin 81mg EC

Active ingredient (in each tablet)

Aspirin 81 mg (NSAID*)

*nonsteroidal anti-inflamatory drug

Purpose

Pain reliever

Uses

temporarily relieves minor aches and pains

Because of its delayed action, this product will not prodice fast relief of headaches or other symptoms needing immediate relief.

ask your doctor about other uses for enteric-coated 81 mg Aspirin

Warnings

Reye's syndrome: Children and teenagers who have or are recoving from chicken pox or flu-like symptoms should not use this product. When using this product, if changes in behavior with nausea and vomiting occur, consult a doctor because these symptoms could be early sign of Reye's syndrome, a rare but serious illness.

Allergy Alert: Aspirin may cause a severe allergic reaction which may include:

- hives

- facial swelling

- shock

- asthma (wheezing)

Stomach bleeding warning: This product contains an NSAID, which may cause severe stomach bleeding. The chance is higher if you:

- are age 60 or older

- have had stomach ulcers or bleeding problems

- take a blood thinning (anticoagulant) or steriod drug

- take other drugs contiaining prescription or nonprescription NSAIDs (aspirin, ibuprofen, naprozen, or others)

- have 3 or more alcoholic drinks every day while using this product

- take more or for longer time than directed

Do not use: if you are allergic to aspirin or any other pain reliver/fever reducer

Ask a doctor or pharmacist before use if you are

- taking a prescription drug for diabetes, gout, or arthritis

- taking any other drug

- under a doctor's care for any serious condition

Stop use and ask a doctor if

- an allergic reaction occurs. Seek medical help right away.

- you are experierance any of the following signs of stomach bleeding: feel faint, have bloody or black stools, vomit blood, have stomach pain that does not get better

- pain gets worse or lasts more than 10 days

- redness or swelling is present

- new symptoms occur

- ringing in the ears or a loss of hearing occurs.

these could be signs of a serious condition.

PREGNANCY OR BREAST FEEDING

If pregnant or breast-feeding, ask a health professional before use. It is especially important not to use aspirin during the last 3 months of pregnancy unless definitely directed to do so by a doctor becwause it may cause problems in the unborn child or complications during delivery.

Keep out of reach of children. In case of overdose, get medical help or contact a Poison Control Center right away.

Directions

- Drink a full glass of water with each dose

- adults and children 12 years and over: take 4 to 8 tablets every 4 hours not to exceed 48 tablets in 24 hours unless directed by a doctor

- children under 12 years: consult a doctor

Other information

- store at 25°C (77°F) excursions premitted between 15°-30°C (59°-86°F)

- Use by expiration date on package

Inactive ingredients

corn starch, pregelatinized starch, povidone. microcrystalline cellulose, colloidal silicon dioxide, stearic acid, methacrylic acid and ethyl acrylate copolymer, talc, titanium dioxide, triethyl citrate, colloidal anhydrous silica, sodium bicarbonate, sodium lauryl sulfate, d&c yellow #10

Ask a doctor before use if

stomach bleeding warning applies to you

you have a history of stomach problems, such as heartburn

you have high blood pressure, heart disease, liver cirrhosis, or kidney disease

you are taking a diuretic

you have asthma

you have not been drinking fluids

you have lost a lot of fluid due to vomiting or diarrhea

HOW SUPPLIED

NDC: 71335-1774-8: 15 Tablets in a BOTTLE

NDC: 71335-1774-1: 120 Tablets in a BOTTLE

NDC: 71335-1774-2: 30 Tablets in a BOTTLE

NDC: 71335-1774-3: 100 Tablets in a BOTTLE

NDC: 71335-1774-4: 20 Tablets in a BOTTLE

NDC: 71335-1774-5: 90 Tablets in a BOTTLE

NDC: 71335-1774-6: 60 Tablets in a BOTTLE

NDC: 71335-1774-7: 36 Tablets in a BOTTLE

Repackaged/Relabeled by:

Bryant Ranch Prepack, Inc.

Burbank, CA 91504

PACKAGE LABEL

Aspirin 81 mg EC Tablet